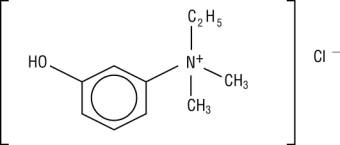 DRUG LABEL: Unknown
Manufacturer: Baxter Healthcare Corporation
Category: prescription | Type: HUMAN PRESCRIPTION DRUG LABELING
Date: 20061017

ENLON (edrophonium chloride injection, USP)
Rx only

DESCRIPTION

ENLON is a short and rapid-acting cholinergic drug. Chemically, edrophonium chloride is ethyl(m-hydroxyphenyl) dimethylammonium chloride and its structural formula is:

Each mL contains, in a sterile solution, 10 mg edrophonium chloride compounded with 0.45% phenol as a preservative, and 0.2% sodium sulfite as an antioxidant, buffered with sodium citrate and citric acid, and pH adjusted to approximately 5.4.

ENLON is intended for IV and IM use.

ACTIONS

ENLON is an anticholinesterase drug. Its pharmacologic action is due primarily to the inhibition or inactivation of acetylcholinesterase at sites of cholinergic transmission. Its effect is manifest within 30 to 60 seconds after injection and lasts an average of 10 minutes.

INDICATIONS

ENLON is recommended for the differential diagnosis of myasthenia gravis and as an adjunct in the evaluation of treatment requirements in this disease. It may also be used for evaluating emergency treatment in myasthenic crises. Because of its brief duration of action, it is not recommended for maintenance therapy in myasthenia gravis.

ENLON is also useful whenever a curare antagonist is needed to reverse the neuromuscular block produced by curare, tubocurarine, gallamine triethiodide or dimethyl-tubocurarine. It is not effective against decamethonium bromide and succinylcholine chloride. It may be used adjunctively in the treatment of respiratory depression caused by curare overdosage.

CONTRAINDICATIONS

Known hypersensitivity to anticholinesterase agents; intestinal and urinary obstructions of mechanical type.

WARNINGS

Whenever anticholinesterase drugs are used for testing, a syringe containing 1 mg of atropine sulfate should be immediately available to be given in aliquots intravenously to counteract severe cholinergic reactions which may occur in the hypersensitive individual, whether he is normal or myasthenic. ENLON should be used with caution in patients with bronchial asthma or cardiac dysrhythmias. The transient bradycardia which sometimes occurs can be relieved by atropine sulfate. Isolated instances of cardiac and respiratory arrest following administration of ENLON have been reported. It is postulated that these are vagotonic effects.

Contains sodium sulfite, a sulfite that may cause allergic-type reactions including anaphylactic symptoms and life-threatening or less severe asthmatic episodes in certain susceptible people. The overall prevalence of sulfite sensitivity in the general population is unknown and probably low. Sulfite sensitivity is seen more frequently in asthmatic than in nonasthmatic people.

Usage in Pregnancy

The safety of ENLON during pregnancy or lactation in humans has not been established. Therefore, use of ENLON in women who may become pregnant requires weighing the drug’s potential benefits against its possible hazards to mother and child.

PRECAUTIONS

Patients may develop “anticholinesterase insensitivity” for brief or prolonged periods. During these periods the patients should be carefully monitored and may need respiratory assistance. Dosages of anticholinesterase drugs should be reduced or withheld until patients again become sensitive to them.

ADVERSE REACTIONS

Careful observation should be made for severe cholinergic reactions in the hyperreactive individual. The myasthenic patient in crisis who is being tested with ENLON should be observed for bradycardia or cardiac standstill and cholinergic reactions if an overdose is given.

The following reactions common to anticholinesterase agents may occur, although not all of these reactions have been reported with the administration of ENLON, probably because of its short duration of action and limited indications:

Eye: | Increased lacrimation, pupillary constriction, spasm of accommodation, diplopia, conjunctival hyperemia.
CNS: | Convulsions, dysarthria, dysphonia, dysphagia.
Respiratory: | Increased tracheobronchial secretions, laryngospasm, bronchiolar constriction, paralysis of muscles of respiration, central respiratory paralysis.
Cardiac: | Arrhythmias (especially bradycardia), fall in cardiac output leading to hypotension.
G.I.: | Increased salivary, gastric and intestinal secretion, nausea, vomiting, increased peristalsis, diarrhea, abdominal cramps.
Skeletal Muscle: | Weakness, fasciculations.
Miscellaneous: | Increased urinary frequency and incontinence, diaphoresis.

DOSAGE AND ADMINISTRATION

ENLON Test in the Differential Diagnosis of Myasthenia Gravis ^1-8

Intravenous Dosage (Adults)

A tuberculin syringe containing 1 mL (10 mg) of ENLON is prepared with an intravenous needle, and 0.2 mL (2 mg) is injected intravenously within 15 to 30 seconds. The needle is left in situ. Only if no reaction occurs after 45 seconds is the remaining 0.8 mL (8 mg) injected. If a cholinergic reaction (muscarinic side effects, skeletal muscle fasciculations and increased muscle weakness) occurs after injection of 0.2 mL (2 mg), the test is discontinued and atropine sulfate, 0.4 mg to 0.5 mg, is administered intravenously. After one-half hour the test may be repeated.

Intramuscular Dosage (Adults)

In adults with inaccessible veins, dosage for intramuscular injection is 1 mL (10 mg) of ENLON. Subjects who demonstrate hyperreactivity to this injection (cholinergic reaction), should be retested after one-half hour with 0.2 mL (2 mg) of ENLON intramuscularly to rule out false-negative reactions.

Dosage (Children)

The intravenous testing dose of ENLON in children weighing up to 75 lbs is 0.1 mL (1 mg); above this weight, the dose is 0.2 mL (2 mg). If there is no response after 45 seconds, it may be titrated up to 0.5 mL (5 mg) in children under 75 lbs, given in increments of 0.1 mL (1 mg) every 30 to 45 seconds and up to 1 mL (10 mg) in heavier children. In infants, the recommended dose is 0.05 mL (0.5 mg). Because of technical difficulty with intravenous injection in children, the intramuscular route may be used. In children weighing up to 75 lbs, 0.2 mL (2 mg) is injected intramuscularly. In children weighing more than 75 lbs, 0.5 mL (5 mg) is injected intramuscularly. All signs which would appear with the intravenous test appears with the intramuscular test except that there is a delay of two to ten minutes before a reaction is noted.

ENLON Test for Evaluation of Treatment Requirements in Myasthenia Gravis

The recommended dose is 0.1 mL to 0.2 mL (1 mg to 2 mg) of ENLON, administered intravenously one hour after oral intake of the drug being used in treatment.^1-5 Response will be myasthenic in the undertreated patient, adequate in the controlled patient, and cholinergic in the overtreated patient. Responses to ENLON in myasthenic and nonmyasthenic individuals are summarized in the following chart.

 | Myasthenic [Myasthenic Response- occurs in untreated myasthenics and may serve to establish diagnosis; in patients under treatment, indicates that therapy is inadequate.] | Adequate [Adequate Response- observed in treated patients when therapy is stabilized: a typical response in normal individuals. In addition to this response in non-myasthenics, the phenomenon of forced lid closure is often observed in psychoneurotics.] | Cholinergic [Cholinergic Response- seen in myasthenics who have been overtreated with anticholinesterase drugs.]
Muscle Strength (ptosis, diplopia dysphonia, dysphagia, dysarthria, respiration, limb strength) | Increased | No change | Decreased
Fasciculations (orbicularis oculi, facial muscles, limb muscles) | Absent | Present or absent | Present or absent
Side reactions (lacrimation diaphoresis, salivation, abdominal cramps, nausea, vomiting, diarrhea) | Absent | Minimal | Severe

ENLON Test in Crisis

The term crisis is applied to the myasthenic whenever severe respiratory distress with objective ventilatory inadequacy occurs and the response to medication is not predictable. This state may be secondary to a sudden increase in severity of myasthenia gravis (myasthenic crisis), or to overtreatment with anticholinesterase drugs (cholinergic crisis).

When a patient is apneic, controlled ventilation must be secured immediately in order to avoid cardiac arrest and irreversible central nervous system damage. No attempt is made to test with ENLON until respiratory exchange is adequate.

Dosage used at this time is most important: If the patient is cholinergic, ENLON will cause increased oropharyngeal secretions and further weakness in the muscles of respiration. If the crisis is myasthenic, the test clearly improves respiration and the patient can be treated with longer-acting intravenous anticholinesterase medication. When the test is performed, there should not be more than 0.2 mL (2 mg) ENLON in the syringe. An intravenous dose of 0.1 mL (1 mg) is given initially. The patient’s heart action is carefully observed. If, after an interval of one minute, this dose does not further impair the patient, the remaining 0.1 mL (1 mg) can be injected. If no clear improvement of respiration occurs after 0.2 mL (2 mg) dose, it is usually wisest to discontinue all anticholinesterase drug therapy and secure controlled ventilation by tracheostomy with assisted respiration.^5

For Use as a Curare Antagonist

ENLON should be administered by intravenous injection in 1 mL (10 mg) doses given slowly over a period of 30 to 45 seconds so that the onset of cholinergic reaction can be detected. This dosage may be repeated whenever necessary. The maximal dose for any one patient should be 4 mL (40 mg). Because of its brief effect, ENLON should not be given prior to the administration of curare, tubocurarine, gallamine triethiodide or dimethyl-tubocurarine: it should be used at the time when its effect is needed. When given to counteract curare overdosage, the effect of each dose on the respiration should be carefully observed before it is repeated, and assisted ventilation should always be employed.

Parenteral drug products should be inspected visually for particulate matter and discoloration prior to administration, whenever solution and container permit.

DRUG INTERACTIONS

Care should be given when administering this drug to patients with symptoms of myasthenic weakness who are also on anticholinesterase drugs. Since symptoms of anticholinesterase overdose (cholinergic crisis) may mimic underdosage (myasthenic weakness), their condition may be worsened by the use of this drug. (See OVERDOSAGE section for treatment.)

OVERDOSAGE

With drugs of this type, muscarine-like symptoms (nausea, vomiting, diarrhea, sweating, increased bronchial and salivary secretions and bradycardia) often appear with overdosage (cholinergic crisis). An important complication that can arise is obstruction of the airway by bronchial secretions. These may be managed with suction (especially if tracheostomy has been performed) and by the use of atropine. Many experts have advocated a wide range of dosages of atropine (for ENLON, see atropine dosage below), but if there are copious secretions, up to 1.2 mg intravenously may be given initially and repeated every 20 minutes until secretions are controlled. Signs of atropine overdosage such as dry mouth, flush and tachycardia should be avoided as tenacious secretions and bronchial plugs may form. A total dose of atropine of 5 to 10 mg or even more may be required. The following steps should be taken in the management of overdosage of ENLON:

1. Adequate respiratory exchange should be maintained by assuring an open airway and by the use of assisted respiration augmented by oxygen.
2. Cardiac function should be monitored until complete stabilization has been achieved
3. Atropine sulfate in doses of 0.4 to 0.5 mg should be administered intravenously. This may be repeated every 3 to 10 minutes. Because of the short duration of action of ENLON the total dose required will seldom exceed 2 mg.
4. Pralidoxime chloride (a cholinesterase reactivator) may be given intravenously at the rate of 50 to 100 mg per minute; usually the total dose does not exceed 1000 mg. Extreme caution should be exercised in the use of pralidoxime chloride when the cholinergic symptoms are induced by double-bond phosphorous anticholinesterase drugs. ^9
5. If convulsions occur or shock is present, appropriate measures should be instituted.

HOW SUPPLIED

ENLON (edrophonium chloride injection, USP):

NDC 10019-873-15 | 15 mL vials

ENLON (edrophonium chloride injection, USP) should be stored at controlled room temperature 15º-30ºC (59º-86ºF).

REFERENCES

1. Osserman KE, Kaplan LI. JAMA 1952;150:265.
2. Osserman KE, Kaplan LI., Besson G. J Mt Sinai Hosp 1953;20:165.
3. Osserman KE, Kaplan LI. Arch Neurol Psychiatr 1953;70:385.
4. Osserman KE, Teng P. JAMA 1956;160:153.
5. Osserman KE, Genkins G. Ann Ny Acad Sci 1966;135:312.
6. Tether JE, Second International Symposium Proceedings, Myasthenia Gravis, 1961, p.444.
7. Tether JE, in HF Conn: Current Therapy 1960, Philadelphia, WB Saunders Co, p.551.
8. Tether JE, in HF Conn: Current Therapy 1965, Philadelphia, WB Saunders Co, p.556.
9. Grob D. Johns RJ. JAMA 1958;166:1855.

Baxter and Enlon are trademarks of Baxter International, Inc.

Manufactured for

Baxter Healthcare Corporation

Deerfield, IL 60015 USA

by: Taylor Pharmaceuticals

Decatur, IL 62525

For Product Inquiry 1 800 ANA DRUG (1-800-262-3784)

MLT-46/1.0